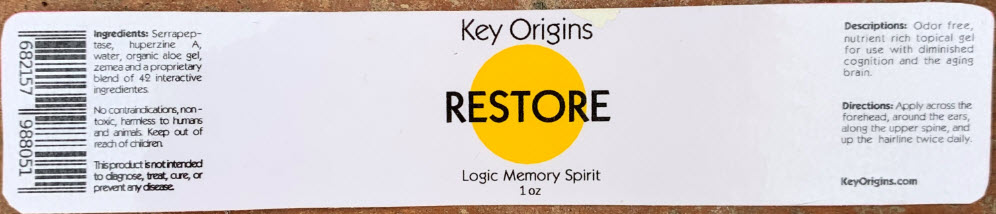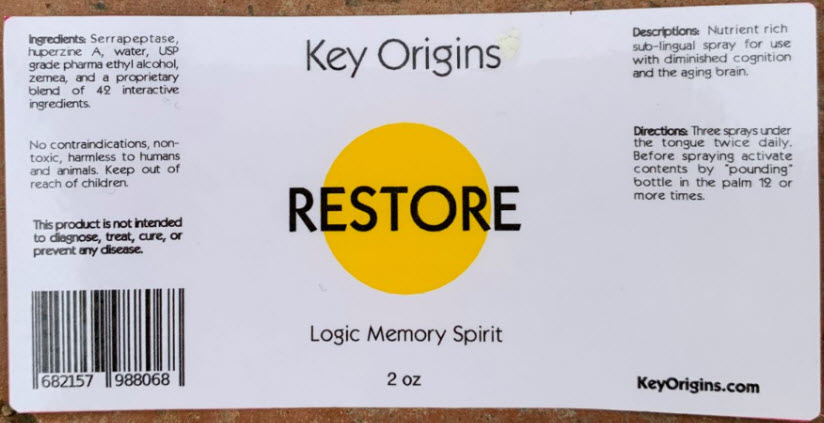 DRUG LABEL: Restore
NDC: 72186-021 | Form: GEL
Manufacturer: Key Origins, Inc.
Category: homeopathic | Type: HUMAN OTC DRUG LABEL
Date: 20191226

ACTIVE INGREDIENTS: Serrapeptase 0.0492 mg/1 mL; Huperzine A 0.0317 mg/1 mL
INACTIVE INGREDIENTS: Water; ALOE VERA LEAF; Propanediol

Restore

RESTORE GEL LABEL:

Ingredients

INACTIVE INGREDIENT

Serrapeptase, huperzine A, water, organic aloe gel, zemea, and a proprietary blend of 42 interactive ingredients.

Descriptions

Odor free nutrient rich topical gel for use with diminished cognition and the aging brain.

No contraindications, non-toxic, harmless to humans and animals.

WARNINGS

Keep out of reach of children.

This product is not intended to diagnose, treat, cure, or prevent any disease.

Directions

PURPOSE

Apply across the forehead, around the ears, along the upper spine, and up the hairline twice daily.

RESTORE SPRAY LABEL:

Ingredients

INACTIVE INGREDIENT

Serrapeptase, huperzine A, water, USP grade pharma ethyl alcohol, zemea, and a proprietary blend of 42 interactive ingredients.

No contraindications, non-toxic, harmless to humans and animals.

WARNINGS

Keep out of reach of children.

This product is not intended to diagnose, treat, cure, or prevent any disease.

Descriptions

Nutrient rich sub-lingual spray for use with diminished cognition and the aging brain.

Directions

PURPOSE

Three sprays under the tongue twice daily. Before spraying activate contents by "pounding" bottle in the palm 12 or more times.

PRINCIPAL DISPLAY PANEL - 1 oz Jar Label

Key Origins

RESTORE

Logic Memory Spirit
1 oz

PRINCIPAL DISPLAY PANEL - 2 oz Bottle Label

Key Origins

RESTORE

Logic Memory Spirit

2 oz